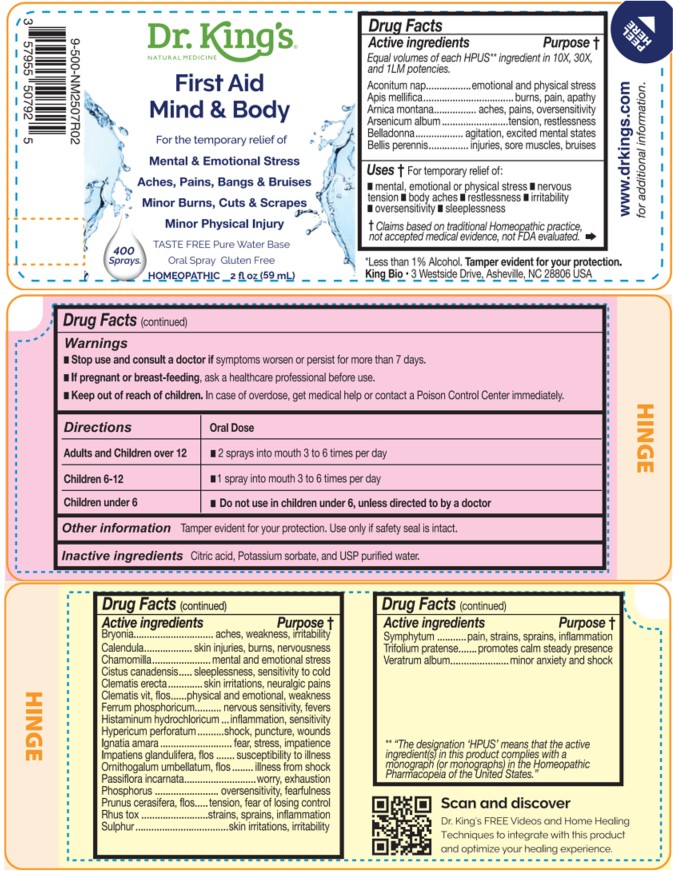 DRUG LABEL: First Aid mind and Body
NDC: 57955-9992 | Form: LIQUID
Manufacturer: King Bio Inc.
Category: homeopathic | Type: HUMAN OTC DRUG LABEL
Date: 20260302

ACTIVE INGREDIENTS: ACONITUM NAPELLUS WHOLE 10 [hp_X]/59 mL; APIS MELLIFERA 10 [hp_X]/59 mL; ARNICA MONTANA WHOLE 10 [hp_X]/59 mL; ARSENIC TRIOXIDE 10 [hp_X]/59 mL; ATROPA BELLADONNA 10 [hp_X]/59 mL; BELLIS PERENNIS WHOLE 10 [hp_X]/59 mL; BRYONIA ALBA ROOT 10 [hp_X]/59 mL; CALENDULA OFFICINALIS FLOWERING TOP 10 [hp_X]/59 mL; MATRICARIA CHAMOMILLA WHOLE 10 [hp_X]/59 mL; CROCANTHEMUM CANADENSE 10 [hp_X]/59 mL; CLEMATIS RECTA FLOWERING TOP 10 [hp_X]/59 mL; CLEMATIS VITALBA FLOWER 10 [hp_X]/59 mL; FERROSOFERRIC PHOSPHATE 10 [hp_X]/59 mL; HISTAMINE DIHYDROCHLORIDE 10 [hp_X]/59 mL; HYPERICUM PERFORATUM WHOLE 10 [hp_X]/59 mL; STRYCHNOS IGNATII SEED 10 [hp_X]/59 mL; IMPATIENS GLANDULIFERA FLOWER 10 [hp_X]/59 mL; ORNITHOGALUM UMBELLATUM FLOWERING TOP 10 [hp_X]/59 mL; PASSIFLORA INCARNATA FLOWERING TOP 10 [hp_X]/59 mL; PHOSPHORUS 10 [hp_X]/59 mL; PRUNUS CERASIFERA FLOWER 10 [hp_X]/59 mL; TOXICODENDRON PUBESCENS LEAF 10 [hp_X]/59 mL; SULFUR 10 [hp_X]/59 mL; COMFREY ROOT 10 [hp_X]/59 mL; TRIFOLIUM PRATENSE FLOWER 10 [hp_X]/59 mL; VERATRUM ALBUM ROOT 10 [hp_X]/59 mL
INACTIVE INGREDIENTS: ANHYDROUS CITRIC ACID; POTASSIUM SORBATE; WATER

First Aid Mind and Body

Active ingredients

Equal volumes of each HPUS** ingredient in 10X,
30X, and 1LM potencies.

Aconitum nap, Apis mellifica, Arnica montana, Arsenicum album, Belladonna, Bellis perennis, Bryonia, Calendula officinalis, Chamomilla, Cistus canadensis, Clematis erecta, Clematis vitalba, flos, Ferrum phosphoricum, Histaminum hydrochloricum, Hypericum perforatum, Ignatia amara, Impatiens glandulifera, flos, Ornithogalum umbellatum, flos, Passiflora incarnata, Phosphorus, Prunus cerasifera, flos, Rhus tox, Sulphur, Symphytum, Trifolium pratense, and Veratrum album.

** "The designation 'HPUS’ means that the active ingredient(s) in this product complies with a monograph (or Monographs) in the Homeopathic Pharmacopeia of the United States.″

INDICATIONS AND USAGE

Uses † For temporary relief of:

- mental
- emotional or physical stress
- nervous tension
- body aches
- restlessness
- irritability
- oversensitivity
- sleeplessness

† Claims based on traditional Homeopathic practice, not accepted medical evidence, not
FDA evaluated.

QUESTIONS

First Aid Mind and Body

HOMEOPATHIC 2 fl oz (59 mL)

TASTE FREE, Pure Water Base*

Oral Spray Gluten Free

*Less than 1% Alcohol Tamper evident for your protection.

Scan and discover Dr. King's FREE Videos and Home Healing
Techniques to integrate with this product and optimize your healing experience.

King Bio, Inc. 3 Westside Drive

Asheville, NC 28806 USA

www.DrKings.com for additional information.

Warnings

- Stop use and consult a doctor if symptoms worsen or persist for more than 7 days.
- If pregnant or breast-feeding, ask a healthcare professional before use.

- Keep out of reach of children. In case of overdose, get medical help or contact a Poison Control Center immediately.

DOSAGE AND ADMINISTRATION

Directions | Oral Dose
Adults and Children over 12 | - 2 sprays into mouth 3 to 6 times per day
Children 6-12 | - 1 spray into mouth 3 to 6 times per day
Children under 6 | - Do not use in children under 6, unless directed to by a doctor

Other information

Tamper evident for your protection.

Use only if safety seal is intact.

Inactive Ingredients

Citric acid, Potassium sorbate, and USP purified water.

PURPOSE

Equal volumes of each HPUS** ingredient in 10X, 30X, and 1LM potencies.

Active ingredients Purpose †

Aconitum nap..........................................emotional and physical stress
Apis mellifica ........................................................burns, pain, apathy
Arnica montana ........................................aches, pains, oversensitivity
Arsenicum album ................................................tension, restlessness
Belladonna ..........................................agitation, excited mental states
Bellis perennis .......................................injuries, sore muscles, bruises
Bryonia ....................................................aches, weakness, irritability

Calendula officinalis .............................skin injuries, burns, nervousness
Chamomilla...............................................mental and emotional stress
Cistus canadensis.................................sleeplessness, sensitivity to cold
Clematis erecta ......................................skin irritations, neuralgic pains
Clematis vitalba, flos ..........................physical and emotional, weakness
Ferrum phosphoricum.....................................nervous sensitivity, fevers
Histaminum hydrochloricum...............................inflammation, sensitivity
Hypericum perforatum.....................................shock, puncture, wounds
Ignatia amara....................................................fear, stress, impatience
Impatiens glandulifera, flos...................................susceptibility to illness
Ornithogalum umbellatum, flos....................................illness from shock
Passiflora incarnata....................................................worry, exhaustion
Phosphorus...................................................oversensitivity, fearfulness
Prunus cerasifera, flos.................................tension, fear of losing control
Rhus tox...................................................strains, sprains, inflammation
Sulphur ..........................................................skin irritations, irritability
Symphytum officinale ........................pain, strains, sprains, inflammation
Trifolium pratense ..................................promotes calm steady presence
Veratrum album................................................minor anxiety and shock

** "The designation 'HPUS’ means that the active ingredient(s) in this product complies with a monograph (or Monographs) in the Homeopathic Pharmacopeia of the United States.″

† Claims based on traditional Homeopathic practice, not accepted medical evidence, not
FDA evaluated.